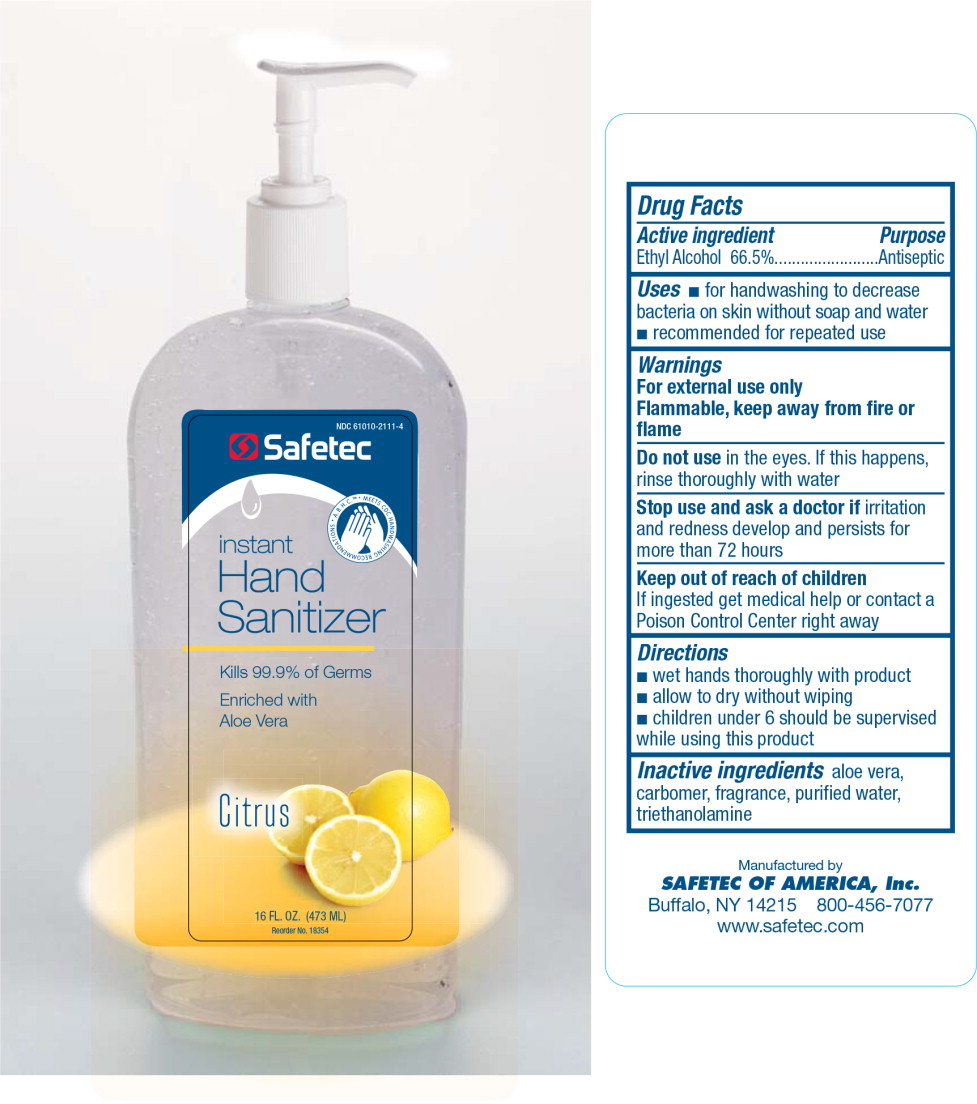 DRUG LABEL: Instant Hand Sanitizer
NDC: 61010-2111 | Form: GEL
Manufacturer: Safetec of America, Inc.
Category: otc | Type: HUMAN OTC DRUG LABEL
Date: 20130517

ACTIVE INGREDIENTS: alcohol 540.26 g/1 L
INACTIVE INGREDIENTS: aloe vera leaf; carbomer interpolymer type a (allyl sucrose crosslinked); water; trolamine

A.B.H.C. INSTANT HAND SANITIZER CITRUS SCENT (alcohol) gel
[Safetec of America, Inc.]

Drug Facts

Active ingredient

Ethyl Alcohol 66.5%

Purpose

Antiseptic

Uses

- for handwashing to decrease bacteria on skin without soap and water
- recommended for repeated use

Warnings

For external use only.

Flammable, keep away from fire or flame

Do not use in the eyes. If this happens, rinse thoroughly with water

Stop use and ask doctor if irritation and redness develop and persists for more than 72 hours

Keep out of reach of children If ingested get medical help or contact a Poison Control Center right away

Directions

- wet hands and wrists thoroughly with product
- allow to dry without wiping
- children under 6 should be supervised while using this product

Inactive ingredients

aloe vera, carbomer, fragrance, purified water, triethanolamine

Principal Display Panel – 16 Fl. OZ. Bottle Label

NDC 61010-2111-4

Safetec

Instant
Hand
Sanitizer

A.B.H.C. ™ MEETS CDC HANDWASHING RECOMMENDATIONS

Kills 99.9% of Germs

Enriched with
Aloe Vera

Citrus

16 FL. OZ. (473 ML)

Reorder No. 18354